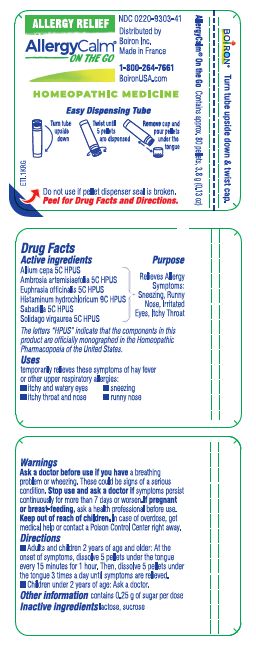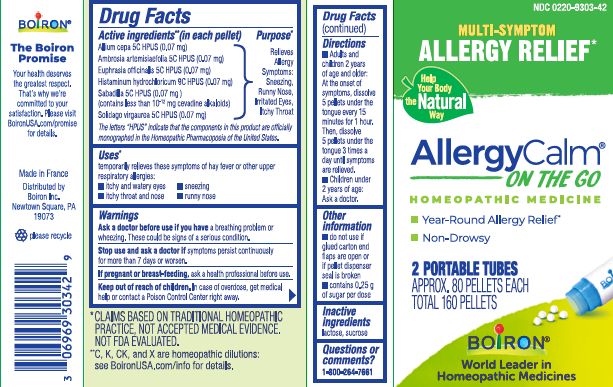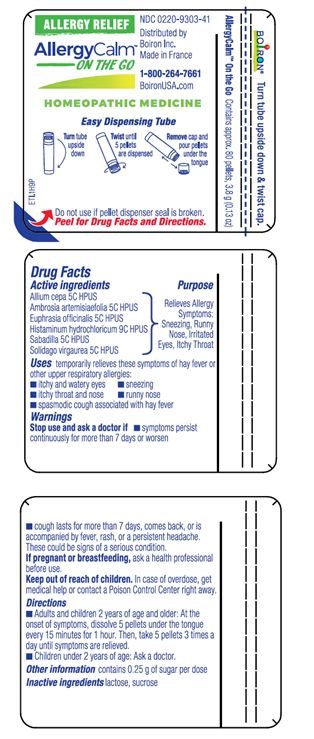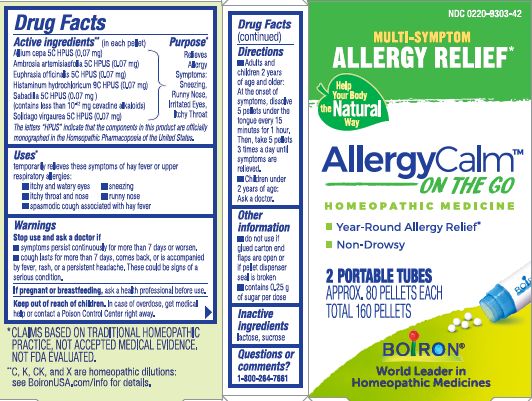 DRUG LABEL: ALLERGYCALM
NDC: 0220-9303 | Form: PELLET
Manufacturer: Boiron
Category: homeopathic | Type: HUMAN OTC DRUG LABEL
Date: 20250512

ACTIVE INGREDIENTS: SOLIDAGO VIRGAUREA FLOWERING TOP 5 [hp_C]/1 1; ONION 5 [hp_C]/1 1; AMBROSIA ARTEMISIIFOLIA 5 [hp_C]/1 1; EUPHRASIA STRICTA 5 [hp_C]/1 1; HISTAMINE DIHYDROCHLORIDE 9 [hp_C]/1 1; SCHOENOCAULON OFFICINALE SEED 5 [hp_C]/1 1
INACTIVE INGREDIENTS: SUCROSE; LACTOSE, UNSPECIFIED FORM

AllergyCalm Pellets

Active Ingredients** (in each pellet)

Allium cepa 5C HPUS (0.07 mg)

Ambrosia artemisiaefolia 5C HPUS (0.07 mg)

Euphrasia officinalis 5C HPUS (0.07 mg)

Histaminum hydrochloricum 9C HPUS (0.07 mg)

Sabadilla 5C HPUS (0.07 mg) (contains less than 10-12 mg cevadine alkaloids)

Solidago vigaurea 5C HPUS (0.07 mg)

The letters "HPUS" indicate that the components in this product are officially monographed in the Homeopathic Pharmacopoeia of the United States.

Purpose*

Relieves Allergy Symptoms: Sneezing, Runny Nose, Irritated Eyes, Itchy Throat

Uses*

temporarily relieves these symptoms of hay fever or upper respiratory allergies:

- itchy and watery eyes
- itchy throat and nose
- sneezing
- runny nose

Ask a doctor before use if you have a breathing problem or wheezing. These could be signs of a serious condition.

Stop use and ask a doctor if symptoms persist continuously for more than 7 days or worsen.

PREGNANCY OR BREAST FEEDING

If pregnant or breast-feeding, ask a health professional before use.

Keep out of reach of children. In case of overdose, get medical help or contact a Poison Control Center right away.

DOSAGE AND ADMINISTRATION

- Adults and children 2 years of age and older: At the onset of symptoms, dissolve 5 pellets under the tongue every 15 minutes for 1 hour. Then, dissolve 5 pellets under the tongue 3 times a day until symptoms are relieved.
- Children under 2 years of age: Ask a doctor.

- do not use if glued carton end flaps are open or if pellet dispenser seal is broken
- contains 0.25 g of sugar per dose

Multi-Symptom Allergy Relief*

Year-Round Allergy Relief*

Non-Drowsy

2 PORTABLE TUBES

APPROX. 80 PELLETS EACH

TOTAL 160 PELLETS

Contains approx. 80 pellets, 3.8 g (0.13 oz)

Turn tube upside down, twist until 5 pellets are dispensed

Remove cap and pour pellets under the tongue

Do not use if pellet dispenser seal is broken.

*CLAIMS BASED ON TRADITIONAL HOMEOPATHIC PRACTICE NOT ACCEPTED MEDICAL EVIDENCE. NOT FDA EVALUATED.
**C,K,CK, and X are homeopathic dilutions: see BoironUSA.com/info for details.

INACTIVE INGREDIENT

lactose, sucrose

QUESTIONS

1-800-264-7661

Made in France

Distributed by

Boiron, Inc.

Newtown Square, PA 19073